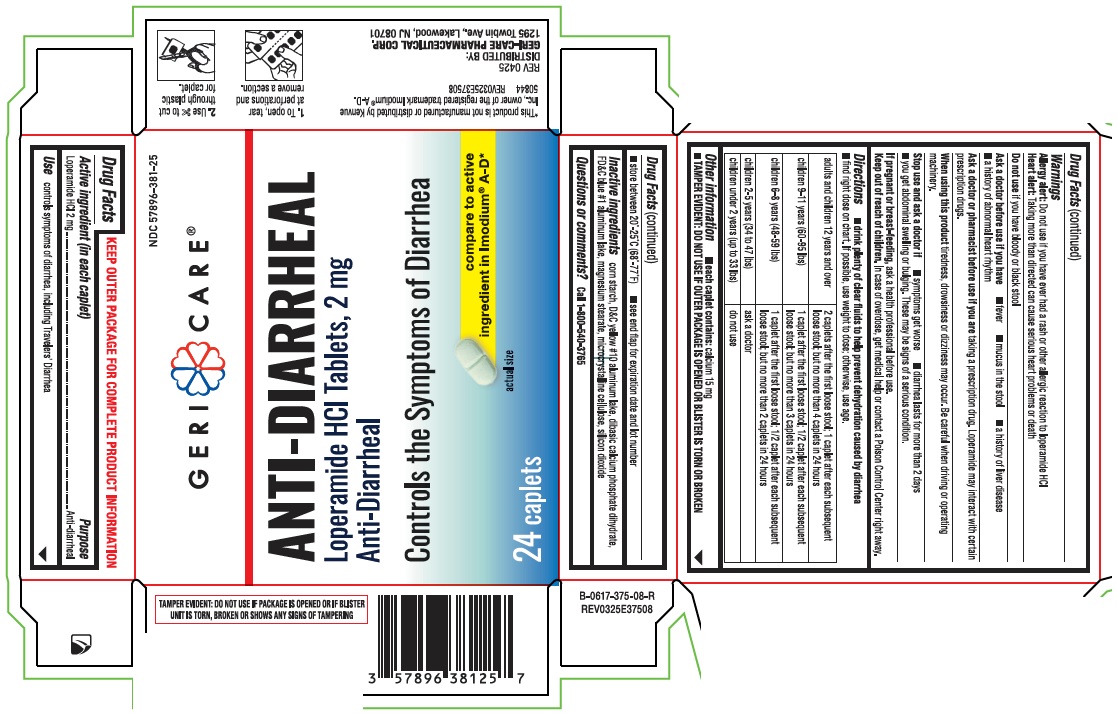 DRUG LABEL: Anti-Diarrheal
NDC: 57896-381 | Form: TABLET
Manufacturer: Geri-Care Pharmaceutical Corp
Category: otc | Type: HUMAN OTC DRUG LABEL
Date: 20250611

ACTIVE INGREDIENTS: LOPERAMIDE HYDROCHLORIDE 2 mg/1 1
INACTIVE INGREDIENTS: STARCH, CORN; D&C YELLOW NO. 10; FD&C BLUE NO. 1; MAGNESIUM STEARATE; SILICON DIOXIDE; CELLULOSE, MICROCRYSTALLINE; DIBASIC CALCIUM PHOSPHATE DIHYDRATE

381

Active ingredient(in each caplet)

Loperamide HCI 2 mg

Purpose

Anti-diarrheal

Uses

controls symptoms of diarrhea, including Travelers' Diarrhea

Warnings

Allergy alert: Do not use if you have ever had a rash or other allergic reaction to loperamide HCI

Heart alert: Taking more than directed can cause serious heart problems or death.

Do not use if you have bloody or black stool

Ask a doctor before use if you have

- a fever
- mucus present in your stool
- a history of liver disease
- a history of abnormal heart rhythm

Ask a doctor or pharmacist before use if you are taking a prescription drug. Loperamide may interact with certain
prescription drugs.

When using this product tiredness, drowsiness or dizziness may occur. Be careful when driving or operating machinery.

Stop use and ask a doctor if

- diarrhea lasts for more than 2 days
- symptoms get worse
- you get abdominal swelling or bulging.

These may be signs of a serious condition.

If pregnant or breast-feeding, ask a health professional before use.

Keep out of reach of children. In case of overdose, get medical
help or contact a Poison Control Center right away.

Directions

- drink plenty of clear fluids to help prevent dehydration caused by diarrhea
- find right dose on chart. If possible, use weight to dose; otherwise, use age.

adults and children 12 years and over | 2 caplets after the first loose stool; 1 caplet after each subsequent loose stool; but no more than 4 caplets in 24 hours
children 9-11 years (60-95 lbs) | 1 caplet after the first loose stool; 1/2 caplet after each subsequent loose stool; but no more than 3 caplets in 24 hours
children 6-8 years (48-59 lbs) | 1 caplet after the first loose stool; 1/2 caplet after each subsequent loose stool; but no more than 2 caplets in 24 hours
children 2-5 years (34-47 lbs) | ask a doctor
children under 2 years (up to 33 lbs) | do not use

Other Information

- each caplet contains: calcium 15 mg
- TAMPER EVIDENT: DO NOT USE IF OUTER PACKAGE IS OPENED OR BLISTER IS TORN OR BROKEN
- store at 20⁰C-25⁰C (68⁰F-77⁰F)
- see end flap for expiration date and lot number

Inactive Ingredients

corn starch, D&C yellow #10 aluminum lake, dibasic calcium phosphate dihydrate,
FD&C blue #1 aluminum lake, magnesium stearate, microcrystalline cellulose, silicon dioxide

Questions or comments?

call 1-800-540-3765